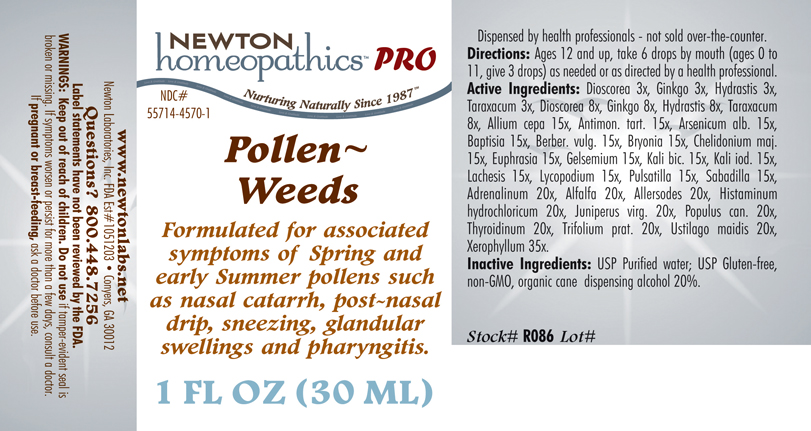 DRUG LABEL: Pollen Weeds 
NDC: 55714-4570 | Form: LIQUID
Manufacturer: Newton Laboratories, Inc.
Category: homeopathic | Type: HUMAN PRESCRIPTION DRUG LABEL
Date: 20110601

ACTIVE INGREDIENTS: Xerophyllum Asphodeloides 35 [hp_X]/1 mL; Epinephrine 20 [hp_X]/1 mL; Alfalfa 20 [hp_X]/1 mL; Aletris Farinosa Root 20 [hp_X]/1 mL; Artemisia Vulgaris Root 20 [hp_X]/1 mL; Bellis Perennis 20 [hp_X]/1 mL; Dysphania Ambrosioides 20 [hp_X]/1 mL; Lycopus Virginicus 20 [hp_X]/1 mL; Phytolacca Americana Root 20 [hp_X]/1 mL; Populus Tremuloides Leaf 20 [hp_X]/1 mL; Populus Tremuloides Bark 20 [hp_X]/1 mL; Ptelea Trifoliata Bark 20 [hp_X]/1 mL; Sambucus Nigra Flowering Top 20 [hp_X]/1 mL; Trillium Erectum Root 20 [hp_X]/1 mL; Elymus Repens Root 20 [hp_X]/1 mL; Urtica Urens 20 [hp_X]/1 mL; Wyethia Helenioides Root 20 [hp_X]/1 mL; Yucca Filamentosa 20 [hp_X]/1 mL; Avena Sativa Pollen 20 [hp_X]/1 mL; Cynosurus Cristatus Pollen 20 [hp_X]/1 mL; Echinochloa Crus-galli Pollen 20 [hp_X]/1 mL; Poa Pratensis Pollen 20 [hp_X]/1 mL; Agrostis Gigantea Pollen 20 [hp_X]/1 mL; Bromus Secalinus Pollen 20 [hp_X]/1 mL; Alopecurus Pratensis Pollen 20 [hp_X]/1 mL; Phleum Pratense Pollen 20 [hp_X]/1 mL; Festuca Pratensis Pollen 20 [hp_X]/1 mL; Holcus Lanatus Pollen 20 [hp_X]/1 mL; Lolium Perenne Pollen 20 [hp_X]/1 mL; Fagus Sylvatica Pollen 20 [hp_X]/1 mL; Betula Pendula Pollen 20 [hp_X]/1 mL; Quercus Alba Pollen 20 [hp_X]/1 mL; Fraxinus Excelsior Pollen 20 [hp_X]/1 mL; Corylus Americana Pollen 20 [hp_X]/1 mL; Populus Nigra Pollen 20 [hp_X]/1 mL; Platanus Orientalis Pollen 20 [hp_X]/1 mL; Ulmus Glabra Pollen 20 [hp_X]/1 mL; Salix Alba Pollen 20 [hp_X]/1 mL; Narcissus Pseudonarcissus 20 [hp_X]/1 mL; Rosa Canina Flower 20 [hp_X]/1 mL; Lilium Candidum Flower 20 [hp_X]/1 mL; Primula Vulgaris 20 [hp_X]/1 mL; Dianthus Caryophyllus Flower 20 [hp_X]/1 mL; Ulex Europaeus Flower 20 [hp_X]/1 mL; Cytisus Scoparius Pollen 20 [hp_X]/1 mL; Calluna Vulgaris Pollen 20 [hp_X]/1 mL; Crataegus Monogyna Pollen 20 [hp_X]/1 mL; Histamine Dihydrochloride 20 [hp_X]/1 mL; Juniperus Virginiana Twig 20 [hp_X]/1 mL; Populus Balsamifera Leaf Bud 20 [hp_X]/1 mL; Thyroid, Unspecified 20 [hp_X]/1 mL; Trifolium Pratense Flower 20 [hp_X]/1 mL; Ustilago Maydis 20 [hp_X]/1 mL; Onion 15 [hp_X]/1 mL; Antimony Potassium Tartrate 15 [hp_X]/1 mL; Arsenic Trioxide 15 [hp_X]/1 mL; Baptisia Tinctoria Root 15 [hp_X]/1 mL; Berberis Vulgaris Root Bark 15 [hp_X]/1 mL; Bryonia Alba Root 15 [hp_X]/1 mL; Chelidonium Majus 15 [hp_X]/1 mL; Euphrasia Stricta 15 [hp_X]/1 mL; Gelsemium Sempervirens Root 15 [hp_X]/1 mL; Potassium Dichromate 15 [hp_X]/1 mL; Potassium Iodide 15 [hp_X]/1 mL; Lachesis Muta Venom 15 [hp_X]/1 mL; Lycopodium Clavatum Spore 15 [hp_X]/1 mL; Pulsatilla Vulgaris 15 [hp_X]/1 mL; Schoenocaulon Officinale Seed 15 [hp_X]/1 mL; Dioscorea Villosa Tuber 8 [hp_X]/1 mL; Ginkgo 8 [hp_X]/1 mL; Goldenseal 8 [hp_X]/1 mL; Taraxacum Officinale 8 [hp_X]/1 mL; Anthoxanthum Odoratum Pollen 20 [hp_X]/1 mL
INACTIVE INGREDIENTS: Water; Alcohol

Pollen - Weeds

INDICATIONS & USAGE SECTION

Formulated for associated symptoms of Spring and early Summer pollens such as nasal catarrh, post-nasal drip, sneezing, glandular swellings and pharyngitis.

DOSAGE & ADMINISTRATION SECTION

Directions: Ages 12 and up, take 6 drops by mouth (ages 0 to 11, give 3 drops) as needed or as directed by a health professional.

OTC - ACTIVE INGREDIENT SECTION

Xerophyllum asphodeloides 35, Adrenalinum 20x, Alfalfa 20x, Allersodes 20x, Histaminum hydrochloricum 20x, Juniperus virg. 20x, Populus can. 20x, Thyroidinum 20x, Trifolium prat. 20x, Ustilago maidis 20x, Allium cepa 15x, Antimon. tart. 15x, Arsenicum alb. 15x, Baptisia 15x, Berber. vulg. 15x, Bryonia 15x, Chelidonium majus 15x, Euphrasia 15x, Gelsemium 15x, Kali bic. 15x, Kali iod. 15x, Lachesis 15x, Lycopodium 15x, Pulsatilla 15x, Sabadilla 15x, Dioscorea 8x, Ginkgo 8x, Hydrastis 8x, Taraxacum 8x, Dioscorea 3x, Ginkgo 3x, Hydrastis 3x, Taraxacum 3x.

OTC - PURPOSE SECTION

Formulated for associated symptoms of Spring and early Summer pollens such as nasal catarrh, post-nasal drip, sneezing, glandular swellings and pharyngitis.

INACTIVE INGREDIENT SECTION

Inactive Ingredients: USP Purified Water; USP Gluten-free, non-GMO, organic cane dispensing alcohol 20%.

QUESTIONS SECTION

www.newtonlabs.net Newton Laboratories, Inc. FDA Est # 1051203 - Conyers, GA 30012
Questions? 1.800.448.7256

WARNINGS SECTION

Warnings: Keep out of reach of children. Do no use if tamper-evident seal is broken or missing. If symptoms worsen or persist for more than a few days, consult a doctor. If pregnant or breast-feeding, ask a doctor before use.

OTC - PREGNANCY OR BREAST FEEDING SECTION

If pregnant or breast-feeding, ask a doctor before use.

OTC - KEEP OUT OF REACH OF CHILDREN SECTION

Keep out of reach of children.